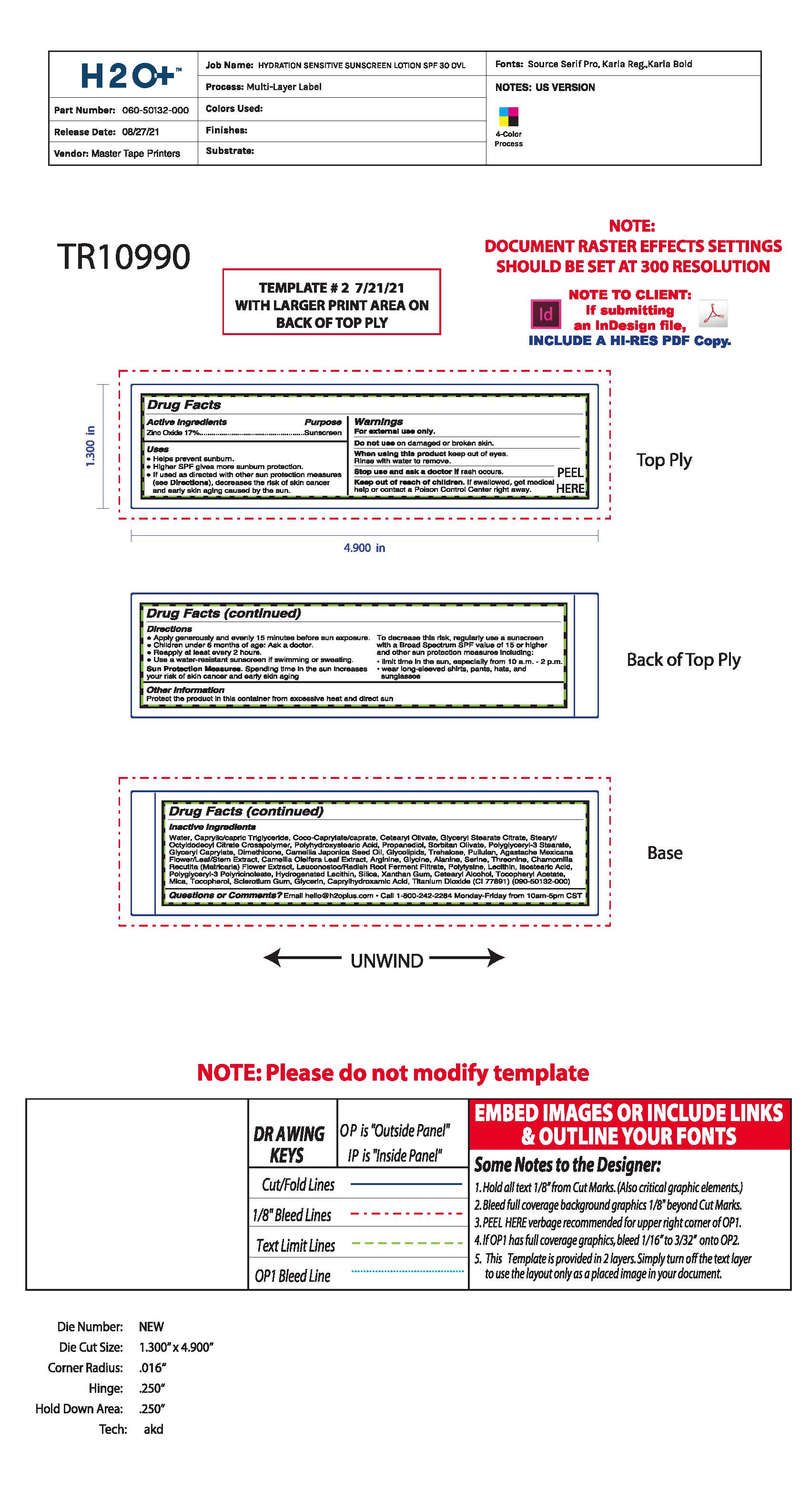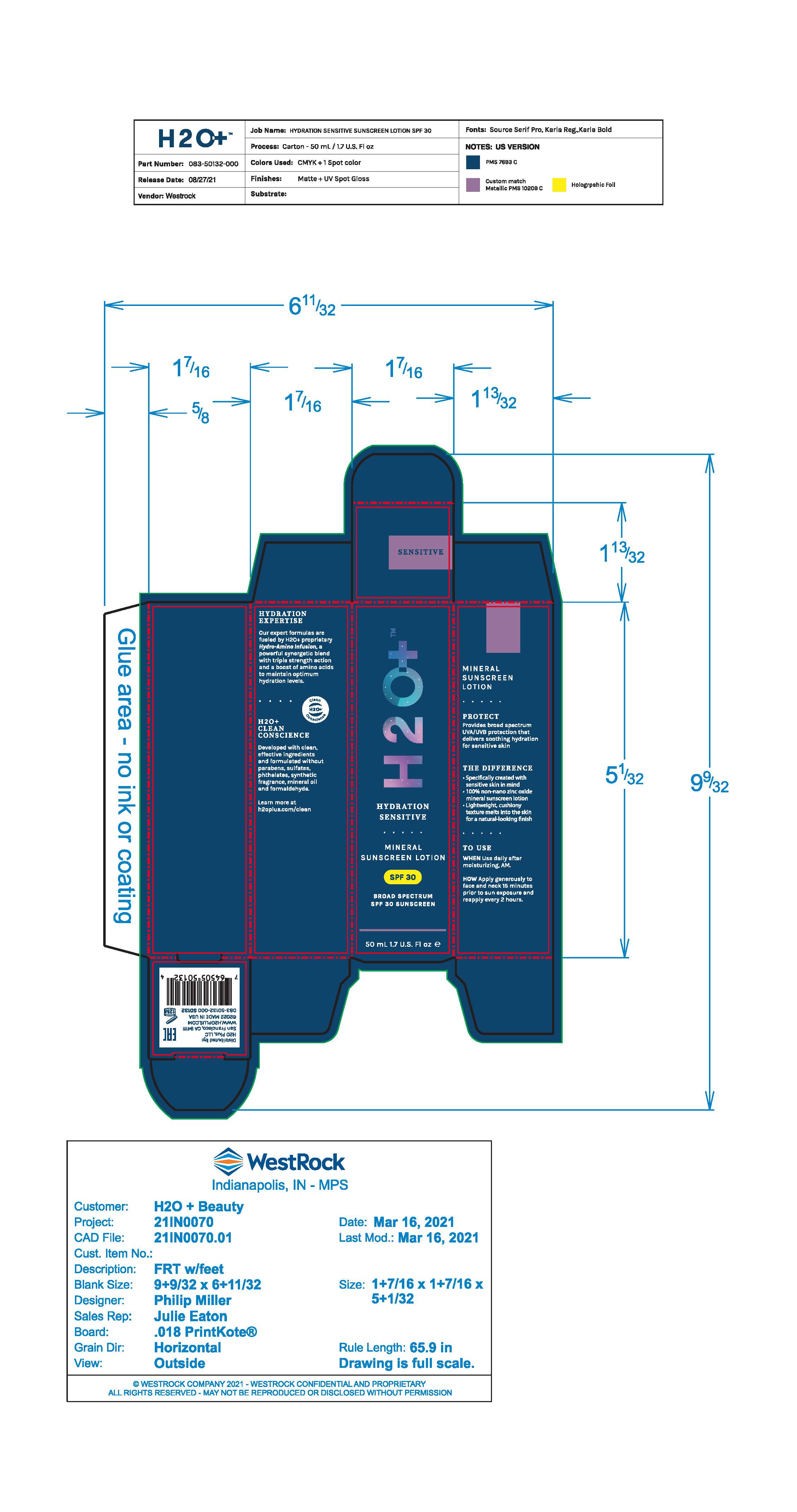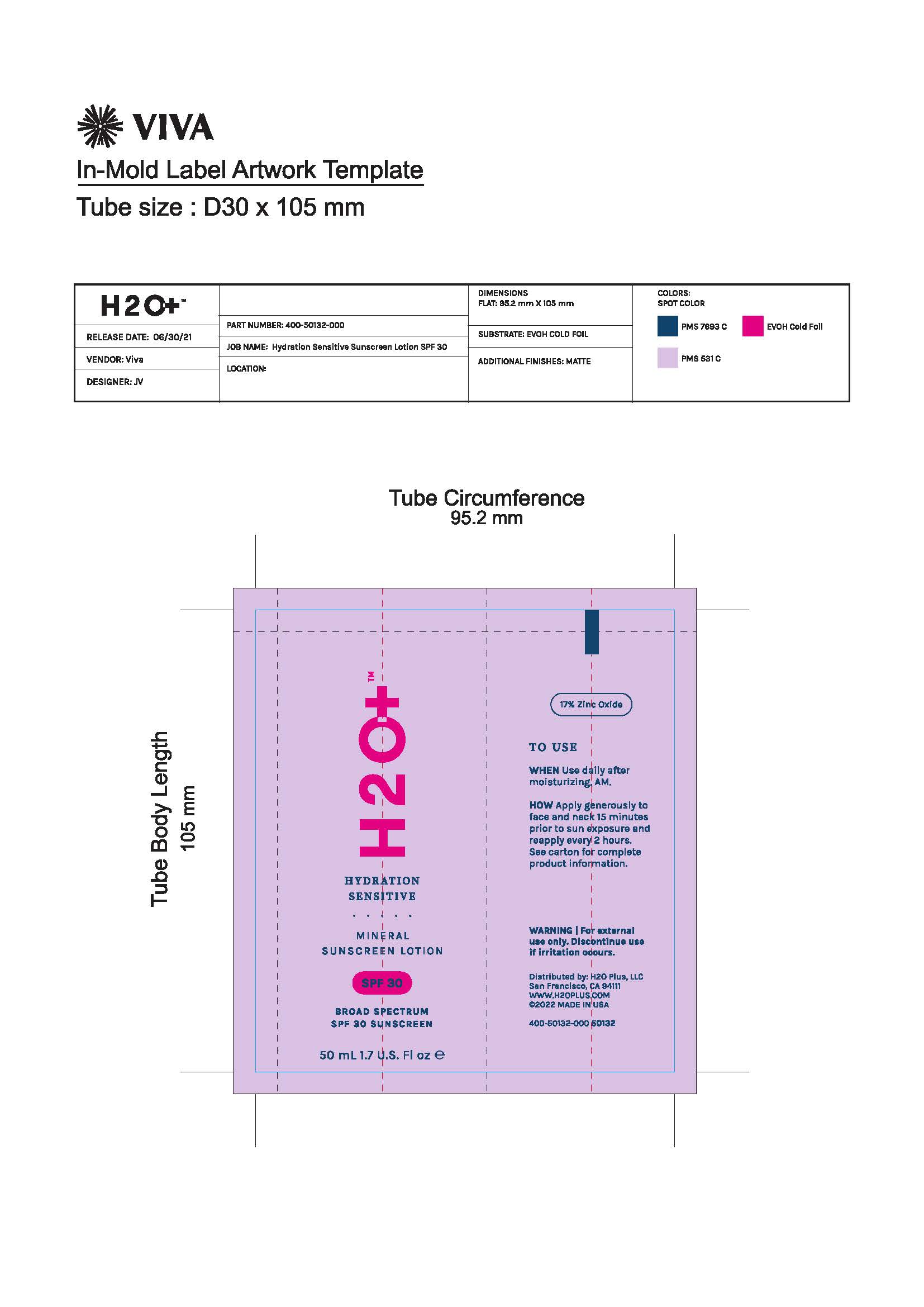 DRUG LABEL: Moisturizer
NDC: 61354-042 | Form: LOTION
Manufacturer: Oxygen Development LLC
Category: otc | Type: HUMAN OTC DRUG LABEL
Date: 20220104

ACTIVE INGREDIENTS: ZINC OXIDE 17.68 mg/100 mg
INACTIVE INGREDIENTS: COCO-CAPRYLATE/CAPRATE 5 mg/100 mg; SORBITAN OLIVATE 1.52 mg/100 mg; POLYGLYCERYL-3 STEARATE 1.2 mg/100 mg; HYDROGENATED SOYBEAN LECITHIN 0.6 mg/100 mg; SILICON DIOXIDE 0.51 mg/100 mg; DIMETHICONE 1 mg/100 mg; ISOSTEARIC ACID 0.78 mg/100 mg; PROPANEDIOL 1.6 mg/100 mg; POLYGLYCERYL-3 PENTARICINOLEATE 0.78 mg/100 mg; GLYCERIN 0.65 mg/100 mg; WATER 51.72 mg/100 mg; MEDIUM-CHAIN TRIGLYCERIDES 5.2 mg/100 mg; STEARYL/OCTYLDODECYL CITRATE CROSSPOLYMER 2 mg/100 mg; POLYHYDROXYSTEARIC ACID (2300 MW) 1.78 mg/100 mg; GLYCERYL STEARATE CITRATE 2.19 mg/100 mg; LECITHIN, SUNFLOWER 0.88 mg/100 mg; CETEARYL OLIVATE 2.28 mg/100 mg; GLYCERYL CAPRYLATE 1.12 mg/100 mg

H2O+ Hydration Sensitive Sunscreen Lotion SPF 30 Broad Spectrum SPF 30 Sunscreen

Active ingredient

Zinc Oxide 17%

Purpose

Sunscreen

Uses

helps prevent sunburn protection. Higher SPF gives more sunburn protection. If used as directed with other sun protection measures (see Directions) decreases the risk of skin cancer and early skin aging caused by the sun.

Warnings

For external use only.

Do not use on damage or broken skin.

When using

When using this product keep out of eyes. Rinse with water to remove.

Stop use

Stop use and ask a dosctor if rash occurs.

Keep out the reach of children. If swallowed, get medical help or contact a Poison Control Center right away.

Directions

Apply generously and evenly 15 minutes before sun exposure.

Children under 6 months of age: Ask a doctor.

Reapply at least every 2 hours.

use a water resistant sunscreen if swimming or sweating.

Sun protection measures. Spending time in the sun increases your risk of skin cancer and early skin aging. To decrease thsi risk, regulary use a sunscreen with a Board Spectrum SPF value of 15 or higher and other sun protection measures including: limit time in the sun, especially from 10 a.m - 2 p.m. wear long - sleeved shirts, pants, hats, and sunglasses

Other information

Protect the protect in this container from excessive heat and direct sun

Inactive ingredients

Water, Caprylic/Capric Triglyceride, Coco-Caprylate/Caprate, Cetearyl Olivate, Glyceryl Stearate Citrate, Stearyl/Octyldodecyl Citrate Crosspolymer, Dimethicone, Camellia Japonica Seed Oil, Glycolipids, Trehalose, Pullulan, Agastache Mexicana Flower/Leaf/Stem Extract, Camellia Oleifera Leaf Extract, Glycine, Alanine, Serine, Threonine, Chamomilla Recutita (Matricaria) Flower Extract, Leuconostoc/Radish Root Ferment Filtrate, Polylysine, Lecithin, Isostearic Acid, Polyglyceryl-3 Polyricinoleate, Hydrogenated Lecithin, Silica, Xanthan Gum, Cetearyl Alcohol, Tocopheryl Acetate, Mica, Tocopheryl, Sclerotium Gum, Glycerin, Caprylhydroxamic Acid, Titanium Dioxide (CI 77891) (090-50132-000)